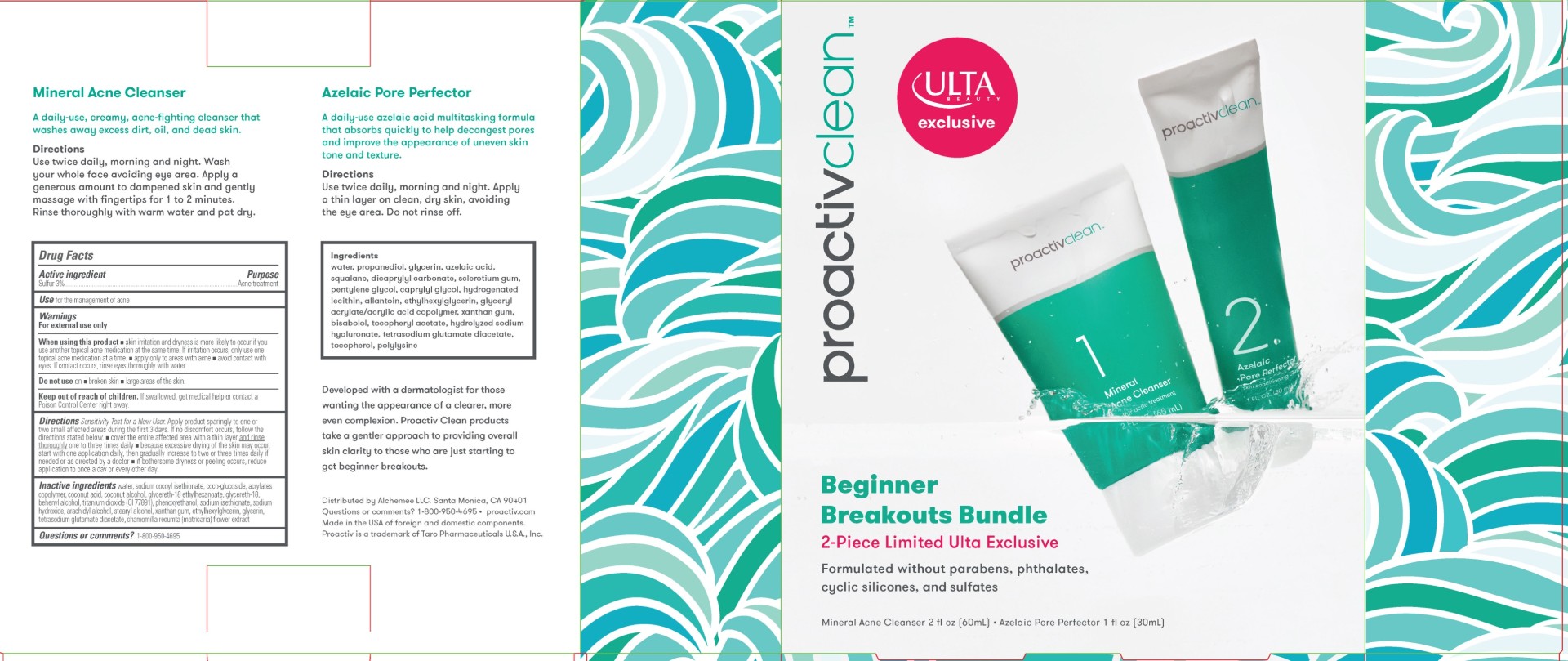 DRUG LABEL: Proactiv Clean Beginner Bundle
NDC: 11410-229 | Form: KIT | Route: TOPICAL
Manufacturer: Alchemee, LLC
Category: otc | Type: HUMAN OTC DRUG LABEL
Date: 20260107

ACTIVE INGREDIENTS: SULFUR 3 g/100 mL
INACTIVE INGREDIENTS: GLYCERETH-18 ETHYLHEXANOATE; WATER; SODIUM COCOYL ISETHIONATE; GLYCERETH-18; TETRASODIUM GLUTAMATE DIACETATE; COCONUT ACID; ETHYLHEXYLGLYCERIN; COCO GLUCOSIDE; MATRICARIA CHAMOMILLA; DOCOSANOL; GLYCERIN; COCONUT ALCOHOL; TITANIUM DIOXIDE; ARACHIDYL ALCOHOL; SODIUM ISETHIONATE; SODIUM HYDROXIDE; STEARYL ALCOHOL; PHENOXYETHANOL; XANTHAN GUM

Proactiv Clean Beginner Kit

Mineral Acne Cleanser - Drug Facts

Drug Facts

Mineral Acne Cleanser - Active ingredient

Sulfur 3%

Mineral Acne Cleanser - Purpose

Acne treatment

Mineral Acne Cleanser - Use

for the management of acne

Mineral Acne Cleanser - Warnings

For external use only

Mineral Acne Cleanser - When using this product

- skin irritation and dryness is more likely to occur if you use another topical acne medication at the same time. If irritation occurs, only use one topical acne medication at a time.
- apply only to areas with acne
- avoid contact with eyes. If contact occurs, rinse eyes thoroughly with water

Mineral Acne Cleanser - Do not use if you

on

- broken skin
- large areas of the skin

Mineral Acne Cleanser - Keep out of reach of children

If swallowed, call a Poison Control Center or get medical help right away.

Mineral Acne Cleanser - Directions

Sensitivity Test for a New User. Apply product sparingly to one or two small affected areas during the first 3 days. If no discomfort occurs follow the directions stated below.

- cover the entire affected area with a thin layer

and rinse thoroughly one to three times daily

- because excessive drying of the skin

may occur, start with one application daily, then gradually increase to two or three times daily if needed or as directed by a doctor

- if bothersome dryness or peeling occurs, reduce application to once a day or every other day.

Mineral Acne Cleanser - Other information

Store at 20oC – 25oC (68o – 77oF).

Mineral Acne Cleanser - Inactive ingredients

Water, Sodium Cocoyl Isethionate, Coco-Glucoside, Acrylates Copolymer, Coconut Acid, Coconut Alcohol, Glycereth-18 Ethylhexanoate, Glycereth-18, Behenyl Alcohol, Titanium Dioxide (CI 77891), Phenoxyethanol, Sodium Isethionate, Sodium Hydroxide, Arachidyl Alcohol, Stearyl Alcohol, Xanthan Gum, Ethylhexylglycerin, Glycerin, Tetrasodium Glutamate Diacetate, Chamomilla Recutita (Matricaria) Flower Extract

Questions or comments?

1-800-950-4695

Distributed by Alchemee LLC
Santa Monica, CA 90401
Made in the USA of Foreign
and Domestic Components
Questions? 1-800-950-4695 • proactiv.com
Proactiv is a registered trademark
of Taro Pharmaceuticals U.S.A., Inc.

PRINCIPAL DISPLAY PANEL - Proactiv Clean Beginner Breakouts Bundle

proactiv®

Proactiv Clean

Beginner

Breakouts Bundle

2-Piece Limited Ulta Exclusive

Formulated without parabens, phthalates,

cyclic silicones, and sulfates

Mineral Acne Cleanser 2 FL. OZ. (60 mL) Azelaic Pore Perfector 1 FL. OZ. (30 mL)